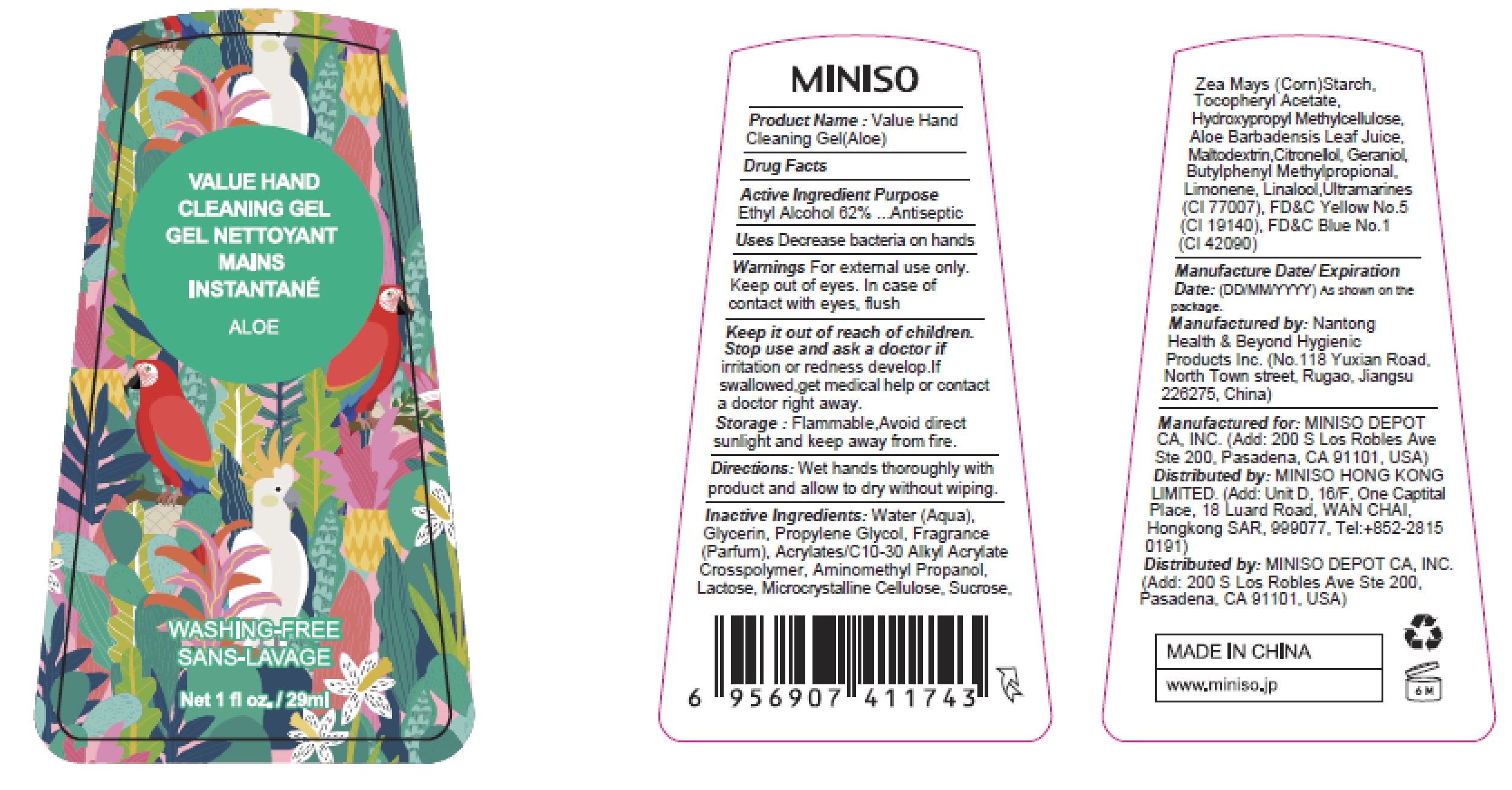 DRUG LABEL: Hand Sanitizer
NDC: 73950-002 | Form: GEL
Manufacturer: MINISO DEPOT CA, INC.
Category: otc | Type: HUMAN OTC DRUG LABEL
Date: 20200524

ACTIVE INGREDIENTS: ALCOHOL 62 mL/100 mL
INACTIVE INGREDIENTS: LIMONENE, (+)-; BUTYLPHENYL METHYLPROPIONAL; FD&C YELLOW NO. 5; GERANIOL; LINALOOL, (+/-)-; ULTRAMARINE BLUE; AMINOMETHYLPROPANOL; FD&C BLUE NO. 1; HYPROMELLOSE, UNSPECIFIED; .ALPHA.-LACTOSE; SUCROSE; MALTODEXTRIN; ALOE VERA LEAF; PROPYLENE GLYCOL; WATER; GLYCERIN; .BETA.-CITRONELLOL, (R)-; MICROCRYSTALLINE CELLULOSE; CARBOMER INTERPOLYMER TYPE A (55000 CPS); .ALPHA.-TOCOPHEROL ACETATE; STARCH, CORN

Active Ingredient
Ethyl Alcohol 62%

Purpose
Antiseptic

INDICATIONS AND USAGE

Uses Decrease bacteria on hands

Warnings For external use only.

Keep out of eyes. In case of contact with eyes, flush

Keep it out of reach of children.

Stop use and ask a doctor if irritation or redness develop.If swallowed,get medical help or contact a doctor right away.

STORAGE AND HANDLING

Storage: Flammable,Avoid direct sunlight and keep away from fire.

DOSAGE AND ADMINISTRATION

Directions: Wet hands thoroughly with product and allow to dry without wiping.

Inactive Ingredients:

Water (Aqua), Glycerin, Propylene Glycol, Fragrance(Parfum), Acrylates/C10-30 Alkyl Acrylate Crosspolymer, Aminomethyl Propanol, Lactose, Microcrystalline Cellulose, Sucrose,Zea Mays (Corn)Starch, Tocopheryl Acetate, Hydroxypropyl Methylcellulose, Aloe Barbadensis Leaf Juice, Maltodextrin,Citronellol, Geraniol, Butylphenyl Methylpropional, Limonene, Linalool,Ultramarines (CI 77007), FD&C Yellow No.5 (CI 19140), FD&C Blue No.1 (CI 42090)